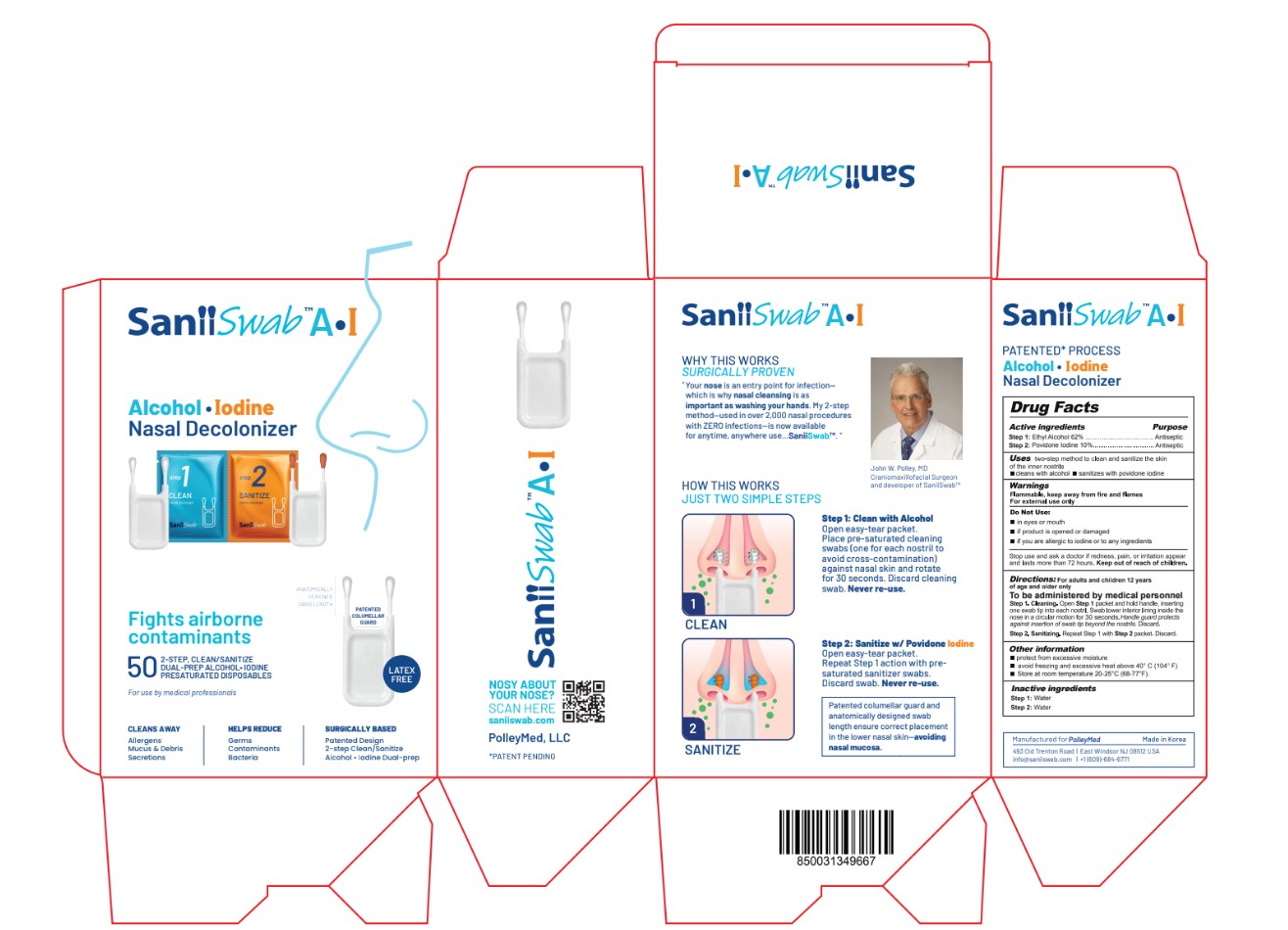 DRUG LABEL: SaniiSwab
NDC: 84456-493 | Form: SWAB
Manufacturer: POLLEY MED LLC
Category: otc | Type: HUMAN OTC DRUG LABEL
Date: 20241108

ACTIVE INGREDIENTS: POVIDONE-IODINE 0.1 g/1 g; ALCOHOL 0.62 g/1 g
INACTIVE INGREDIENTS: WATER

ACTIVE INGREDIENT

Alcohol 62%. Purpose: Antiseptic

Povidone Iodine 10%. Purpose: Antiseptic

PURPOSE

Antiseptic

INDICATIONS AND USAGE

Two-step method to clean and sanitize the skin of the inner nostrils

- Cleans with alcohol
- Sanitizes with povidone iodine

WARNINGS

Flammable, keep away from fire and flames

For external use only

Do Not Use:

- In eyes or mouth
- If product is opened or damaged
- If you are allergic to iodine or to any ingredients

Stop use and ask a doctor if redness, pain, or irritation appear and lasts more than 72 hours. Keep out of reach of children.

DOSAGE AND ADMINISTRATION

For adults and children 12 years of age and older only

To be administered by medical personnel

Step 1. Cleaning. Open Step 1 packet and hold handle, inserting one swab tip into each nostril. Swab lower interior lining inside the nose in a circular motion for 30 seconds. Handle guard protects against insertion of swab tip beyond the nostrils. Discard.

Step 2. Sanitizing. Repeat Step 1 with Step 2 packet. Discard.

STORAGE AND HANDLING

- Protect from excessive moisture
- Avoid freezing and excessive heat above 40°C (104°F)
- Store at room temperature 20-25°C (68-77°F)

INACTIVE INGREDIENT

Water.

Keep out of reach of children.